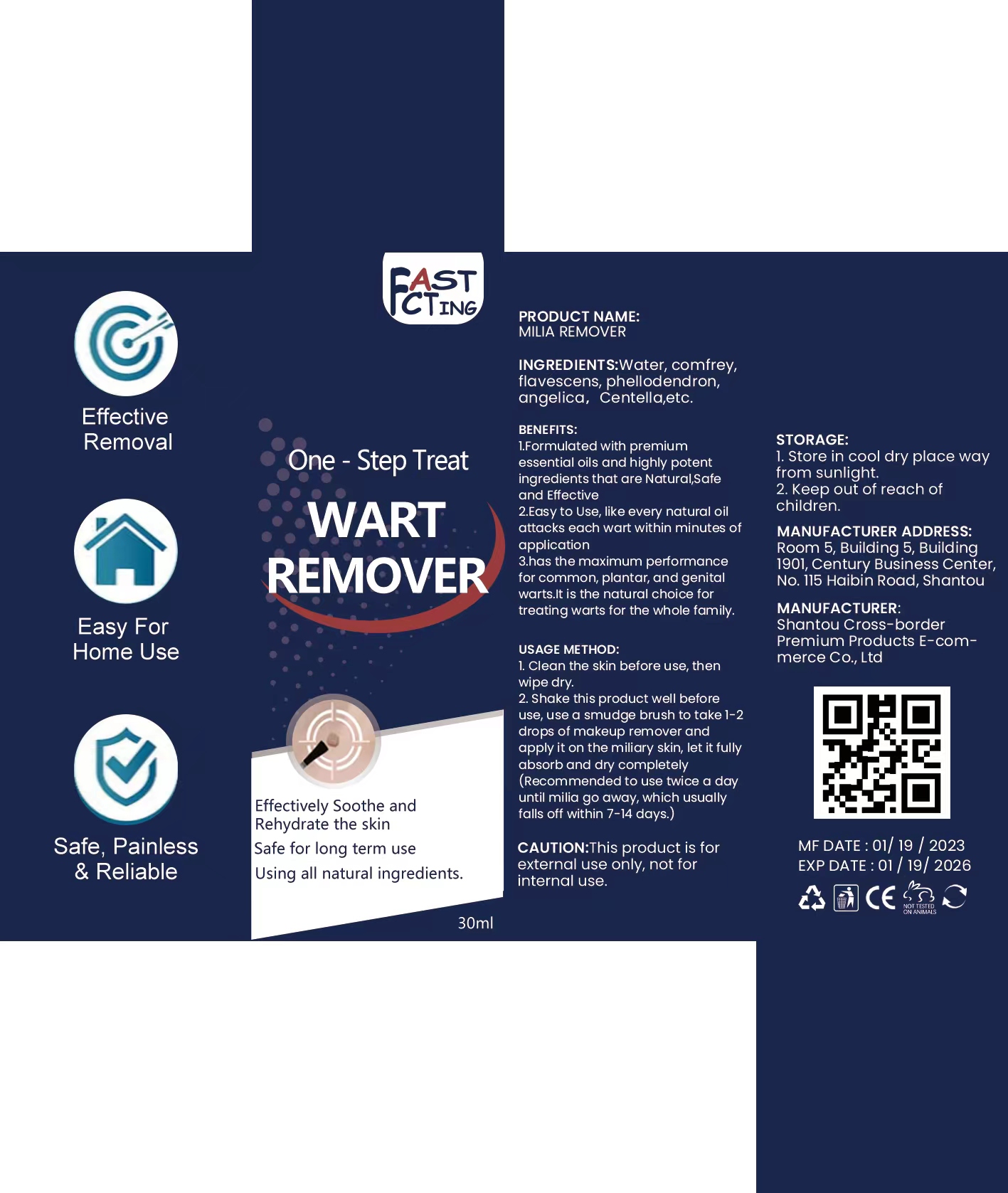 DRUG LABEL: Wart Remover
NDC: 84510-123 | Form: LIQUID
Manufacturer: binzhoutengfenshangmaoyouxiangongsi
Category: otc | Type: HUMAN OTC DRUG LABEL
Date: 20240703

ACTIVE INGREDIENTS: 3,5-DIBROMOSALICYLIC ACID 30 g/100 mL
INACTIVE INGREDIENTS: WATER; WITCH HAZEL; CHLORHEXIDINE ACETATE; TEA TREE OIL; PEPPERMINT

ACTIVE INGREDIENT

Salicylic acid

Chlorhexidine acetate

PURPOSE

has the maximum performance for common, plantar, and genital warts.It is the natural choice for treating warts for the whole family.

Keep out of reach of children.

INACTIVE INGREDIENT

PurifedWater，Witch Hazel ，ExtractPeppermint Extract，TeaTree oil

DOSAGE AND ADMINISTRATION

30ml

1. Clean the skin before use, then wipe dry.

2. Shake this product well before use, use a smudge brush to take 1-2 drops of makeup remover and apply it on the miliary skin, let it fully absorb and dry completely

(Recommended to use twice a day until milia go away, which usually falls off within 7-14 days.)

CAUTION:This product is for external use only, not for internal use.

WARNINGS

1. store in cool dry place way from sunlight
2. Keep out of reach of children.

INDICATIONS AND USAGE

1. Clean the skin before use, then wipe dry.

2. Shake this product well before use, use a smudge brush to take 1-2 drops of makeup remover and apply it on the miliary skin, let it fully absorb and dry completely

(Recommended to use twice a day until milia go away, which usually falls off within 7-14 days.)